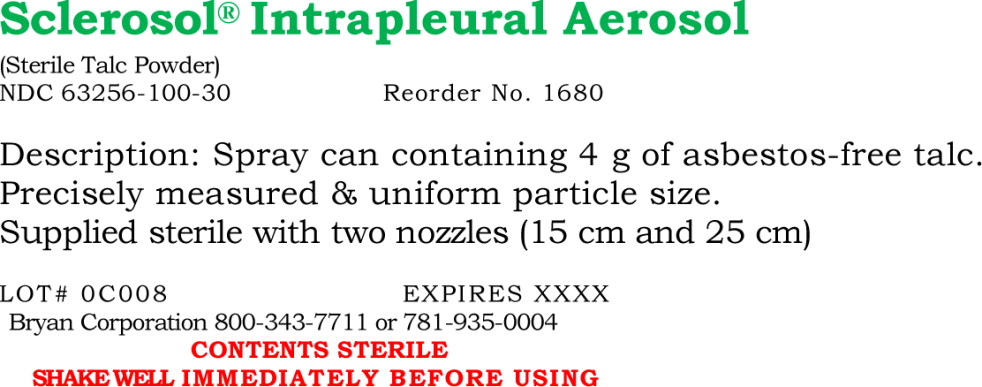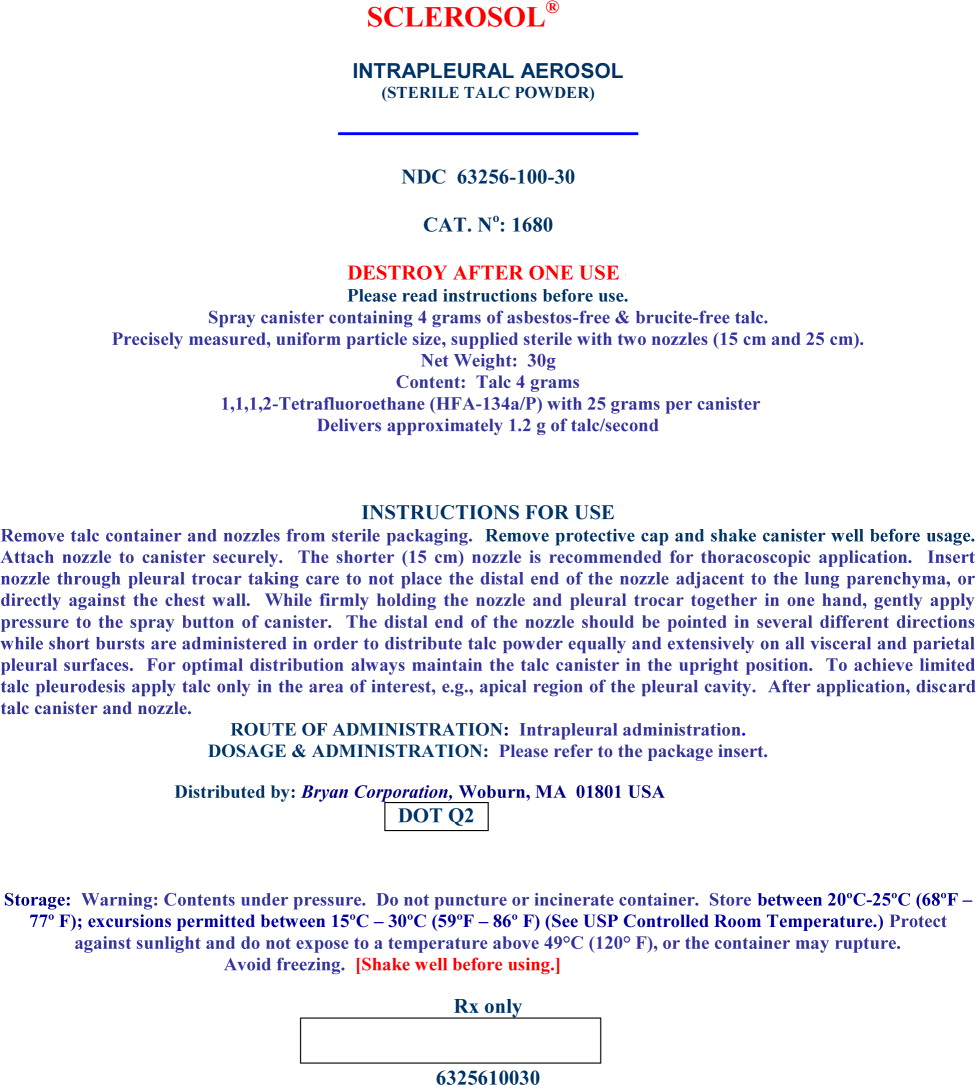 DRUG LABEL: Sclerosol
NDC: 63256-100 | Form: AEROSOL, POWDER
Manufacturer: Bryan Corp
Category: prescription | Type: HUMAN PRESCRIPTION DRUG LABEL
Date: 20121018

ACTIVE INGREDIENTS: Talc 4 g/25.0 g
INACTIVE INGREDIENTS: NORFLURANE

Prescribing Information
SCLEROSOL® INTRAPLEURAL AEROSOL
(sterile talc powder)
NDC No. 63256-100-30

For Intrapleural Administration Only

Shake Well Immediately Before Using

DESCRIPTION

Sclerosol® Intrapleural Aerosol (sterile talc powder 4 g) is a sclerosing agent for intrapleural administration supplied as a single-use, pressurized spray canister with two delivery nozzles of 15 cm and 25 cm in length. Each canister contains 4 g of talc, either white or off-white to light grey, asbestos-free, and brucite-free grade of talc of controlled granulometry. The composition of the talc is ≥ 95% talc as hydrated magnesium silicate. The empirical formula is Mg3Si4O10(OH)2 with molecular weight of 379.3. Associated naturally occurring minerals include chlorite (hydrated aluminum and magnesium silicate), dolomite (calcium and magnesium carbonite), calcite (calcium carbonate) and quartz. Talc is practically insoluble in water, and in dilute solutions of acids and alkali hydroxides. The canister and delivery nozzles have been sterilized by gamma irradiation. The aerosol propellant contained in Sclerosol® Intrapleural Aerosol is 1,1,1,2-Tetrafluoroethane (HFA-134a) with 25 g present per canister. The canister delivers 1.2 g of talc per second through the valve and the product contains no other excipients.

CLINICAL PHARMACOLOGY

Mechanism of Action:

The therapeutic action of talc instilled into the pleural cavity is thought to result from induction of an inflammatory reaction. This reaction promotes adherence of the visceral to the parietal pleura, obliterating the pleural space and preventing reaccumulation of pleural fluid. The extent of talc systemically absorbed after intrapleural administration has not been adequately studied. Systemic exposure could be affected by the integrity of the visceral pleura, and therefore could be increased if talc is administered immediately following lung resection or biopsy.

CLINICAL STUDIES

The data demonstrating safety and efficacy of talc in the treatment of malignant pleural effusions are derived from the published medical literature. The following four trials were prospective, randomized studies of talc vs. a concurrent control, and provide sufficient detail for evaluation, including a clear, readily determined definition of response (no fluid reaccumulation by chest roentgenogram at one month or greater) and information allowing an analysis of all patients randomized. Talc was statistically significantly superior to the control arms in evaluable patients across the studies.

REFERENCE | TREATMENT | TUMOR | RESPONSE RATE IN EVALUABLE PTS p value: Fisher's Exact* | RESPONSE RATE IN ALL PATIENTS p value: Fisher's Exact* | MINIMUM DURATION OF RESPONSE
Sorenson et al. Eur J Respir Dis. 1984; 65:131 | Talc slurry vs Chest tube drainage | Variety | 100% (9/9) vs 58% (7/12) p=0.022 | 64% (9/14) vs 41% (7/17) p=0.285 | 3 months
Fentiman et al . Eur J Cancer Clin Oncol 1986; 22:1079 | Talc poudrage vs Tetracycline solution | Breast | 92% (11/12) vs 48% (10/21) p=0.022 | 61% (11/18) vs 43% (10/23) p=0.345 | 12 months
Fentiman et al . Cancer 1983; 52:737 | Talc poudrage vs Mustine solution | Breast | 90% (18/20) vs 53% (9/17) p=0.023 | 78% (18/23) vs 39% (9/23) p=0.016 | 6 months
Hamed et al . Br. J. Surg 1989; 76:1266 | Talc poudrage vs Bleomycin solution | Breast | 100% (10/10 procedures) vs 33% (5/15 procedures) p=0.001 | (unclear; results reported as procedures, not patients) | ≥1 months
*p values are two-sided

In other studies, greater than 1000 patients with malignant pleural effusions have been reported (with varying degrees of detail and durations of response) to have had successful pleurodesis with talc.

INDICATIONS AND USAGE

Sclerosol® Intrapleural Aerosol, administered by aerosol during thoracoscopy or open thoracotomy, is indicated to prevent recurrence of malignant pleural effusions in symptomatic patients.

CONTRAINDICATIONS

None known.

WARNINGS

None.

PRECAUTIONS

General:

1) Future procedures. The possibility of future diagnostic and therapeutic procedures involving the hemithorax to be treated must be considered prior to administering Sclerosol® Intrapleural Aerosol. Sclerosis of the pleural space may preclude subsequent diagnostic procedures of the pleura on the treated side. Talc sclerosis may complicate or preclude future ipsilateral lung resective surgery, including pneumonectomy for transplantation purposes.

2) Use in potentially curable disease. Talc has no known antineoplastic activity and should not be used for potentially curable malignancies where systemic therapy would be more appropriate, e.g., a malignant effusion secondary to a potentially curable lymphoma.

3) Potential pulmonary complications. Acute pneumonitis or acute respiratory distress syndrome (ARDS) have rarely been reported in association with intrapleural talc administration. Whether these were causally related to talc is unclear. In none of the reported cases was talc applied thoracoscopically or by insufflation. Three of four case reports of ARDS have occurred after treatment with 10 g of talc administered via intrapleural chest tube instillation. One patient died one month post treatment and two patients recovered without further sequelae.

Intravenous administration of talc is a well-recognized cause of pulmonary hypertension and pulmonary lung parenchymal disease, but these complications have not been reported after intrapleural administration. Pulmonary diseases, e.g., silicosis or asbestosis-like diseases, chronic bronchitis, bronchogenic carcinoma, and pleural plaques have been reported in association with inhaled talc.

4) Contents under pressure. The contents of the Sclerosol® Intrapleural Aerosol (sterile talc powder) canister are under pressure. The canister must not be punctured and should not be used or stored near heat or open flame.

DRUG INTERACTIONS

Drug Interactions: It is not known whether the effectiveness of a second sclerosing agent after prior talc pleurodesis would be diminished by the absorptive properties of talc.

CARCINOGENESIS AND MUTAGENESIS AND IMPAIRMENT OF FERTILITY

Carcinogenesis, Mutagenesis, Impairment of Fertility: Studies on the carcinogenicity of talc have been performed using non-standard designs in which talc and its asbestos content were not fully characterized, preventing firm conclusions on its carcinogenicity. Tumor incidence in rats was not increased following either a single 20 mg injection with a 6 month recovery period or weekly injections of 25 mg for 4 weeks with an 84-week recovery period. Genotoxicity was assessed in cultures of rat pleural mesothelial cells (RPMC), as unscheduled DNA syntheses (UDS) and sister chromatid exchanges (SCEs). Asbestos-free talc was negative for genotoxicity under the conditions tested. No information is available on impairment of fertility in animals by talc.

PREGNANCY

Pregnancy: Pregnancy category B. An oral administration study has been performed in the rabbit at 900 mg/kg, approximately 5-fold higher than the human dose on mg/m² basis, and has revealed no evidence of teratogenicity due to talc. There are, however, no adequate and well-controlled studies in pregnant women. Because animal reproduction studies are not always predictive of human response, this drug should not be used during pregnancy unless it is clearly needed.

PEDIATRIC USE

Pediatric Use: The safety and efficacy of Sclerosol Intrapleural Aerosol® (sterile talc powder) in pediatric patients have not been established.

GERIATRIC USE

Geriatric Use: The mean and median ages of patients treated with talc in the clinical studies table were 50-62 years. No analyses to specifically evaluate the safety and efficacy in the geriatric population have been reported.

ADVERSE REACTIONS

Talc administration has been described in more than 1500 patients reported in the medical literature. Patients with malignant pleural effusions were treated with talc via poudrage or slurry. In general, with respect to reported adverse experiences, it is difficult to distinguish the effects of talc from the effects of the procedure(s) associated with its administration. The most reported common adverse experiences were fever and pain. Almost all of the cases of fever, and over half of the cases of pain, were in patients who received diagnostic biopsies at the time of talc administration.

Infections: Empyema was a rare complication of talc administration and/or the procedure. Biopsies had been obtained prior to onset in over half the reported cases.

Respiratory: Rare instances of pneumonia, ARDS, dyspnea, bronchopleural fistula, hemoptysis, and pulmonary emboli have been reported.

Cardiovascular: Tachycardia, myocardial infarction, hypotension, hypovolemia, and asystolic arrest associated with surgery and/or anesthesia have been rarely reported.

Delivery Procedure: Adverse reactions due to the delivery procedure and the chest tube may include: infection at the site of thoracostomy or thoracoscopy, localized bleeding, and subcutaneous empyema.

Chronic Toxicity: Lange et al. (Thorax 1988;43:559) reported on 114 consecutive cases of idiopathic spontaneous pneumothorax treated with talc poudrage (60 patients), or simple drainage (54 patients) via an intercostal tube. Pulmonary function tests (FEV1, VC, TLC, and RV) 22 to 35 years after treatment, showed no significant differences in the incidence of pleural changes between the two groups. Two patients treated with talc poudrage had more extensive pleural thickening with calcification. The mean total lung capacities were 89% of predicted in the talc group and 96% in the drainage only group. Fourteen patients (12 lifelong heavy smokers, 2 non-smokers) had airflow limitation (5 severe). Source and purity of the talc used was not reported. No cases of mesothelioma were reported. One case report noted the occurrence of adenocarcinoma of the chest wall two years after pleurodesis following 10 g of 1% iodized talc (administered for recurrent pneumothorax).

OVERDOSAGE

Overdosages have not been reported. See PRECAUTIONS: 3) Potential pulmonary complications.

DOSAGE AND ADMINISTRATION

Sclerosol® Intrapleural Aerosol (sterile talc powder) is administered after adequate drainage of the effusion. It has been suggested that success of the pleurodesis is related to the completeness of the drainage of the pleural fluid, as well as full reexpansion of the lung, both of which will promote symphysis of the pleural surfaces.

The usual dosage of Sclerosol® Intrapleural Aerosol (sterile talc powder) is a single 4-8 g dose delivered intrapleurally from the spray canister (1-2 cans), which delivers talc at a rate of 1.2 g per second.

ADMINISTRATION PROCEDURE

Shake canister well before usage. Remove protective cap and securely attach actuator button with its delivery nozzle (either 15 cm or 25 cm) to the valve stem of canister.

Insert delivery nozzle through pleural trocar, taking care not to place the distal end of the delivery nozzle adjacent to the lung parenchyma or directly against the chest wall. While firmly holding the delivery nozzle and pleural trocar together in one hand, gently apply pressure to the actuator button on the canister. Sclerosol Intrapleural Aerosol® is not delivered by metered dose, but depends on the extent and duration of manual compression of the actuator button on the canister. The distal end of the delivery nozzle should be pointed in several different directions, while short bursts are administered in order to distribute the talc powder equally and extensively on all visceral and parietal pleural surfaces. For optimal distribution, always maintain the Sclerosol Intrapleural Aerosol® (sterile talc powder) canister in the upright position. After application, discard the canister and delivery nozzle. The duration of chest tube drainage following talc sclerosis is dictated by the clinical situation.

HOW SUPPLIED

NDC 63256-100-30: Sclerosol® Intrapleural Aerosol (sterile talc powder) contains 4 g of talc suspended in 25 g of inert propellant in a single-use aluminum canister. The canister is fitted with a continuous spray valve which delivers approximately 1.2 g of talc per second. This canister, attached to an actuator button, and two delivery nozzles of 15 cm and 25 cm length, are supplied in a sterile, flexible plastic peel pack.

STORAGE AND HANDLING

STORAGE: Warning: Contents under pressure. Do not puncture or incinerate container. Store between 20°C - 25°C (68°F - 77°F); excursions permitted between 15°C - 30°C (59°F - 86°F) (see USP Controlled Room Temperature). Protect against sunlight and do not expose to a temperature above 49° C (120° F), or the canister may rupture. Avoid freezing. Shake well before using.

DISTRIBUTED BY: Bryan Corporation, Woburn MA 01801

October 2012

Principal Display Panel – Pouch Label

Sclerosol® Intrapleural Aerosol
(Sterile Talc Powder)

NDC 63256-100-30 Reorder No. 1680

Description: Spray can containing 4 g of asbestos-free talc.
Precisely measured & uniform particle size.
Supplied sterile with two nozzles (15 cm and 25 cm)

Lot# XXXXX Expires XXXX
Bryan Corporation 800-343-7711 or 781-935-0004
CONTENTS STERILE
SHAKE WELL IMMEDIATELY BEFORE USING

Principal Display Panel – Canister Label

SCLEROSOL®

INTRAPLEURAL AEROSOL
(STERILE TALC POWDER)

NDC 63256-100-30

CAT. No: 1680

DESTROY AFTER ONE USE
Please read instructions before use.
Spray canister containing 4 grams of asbestos-free & brucite-free talc.
Precisely measured, uniform particle size, supplied sterile with two nozzles (15 cm and 25 cm).
Net Weight: 30g
Content: Talc 4 grams
1,1,1,2-Tetrafluoroethane (HFA-134a/P) with 25 grams per canister
Delivers approximately 1.2 g of talc/second